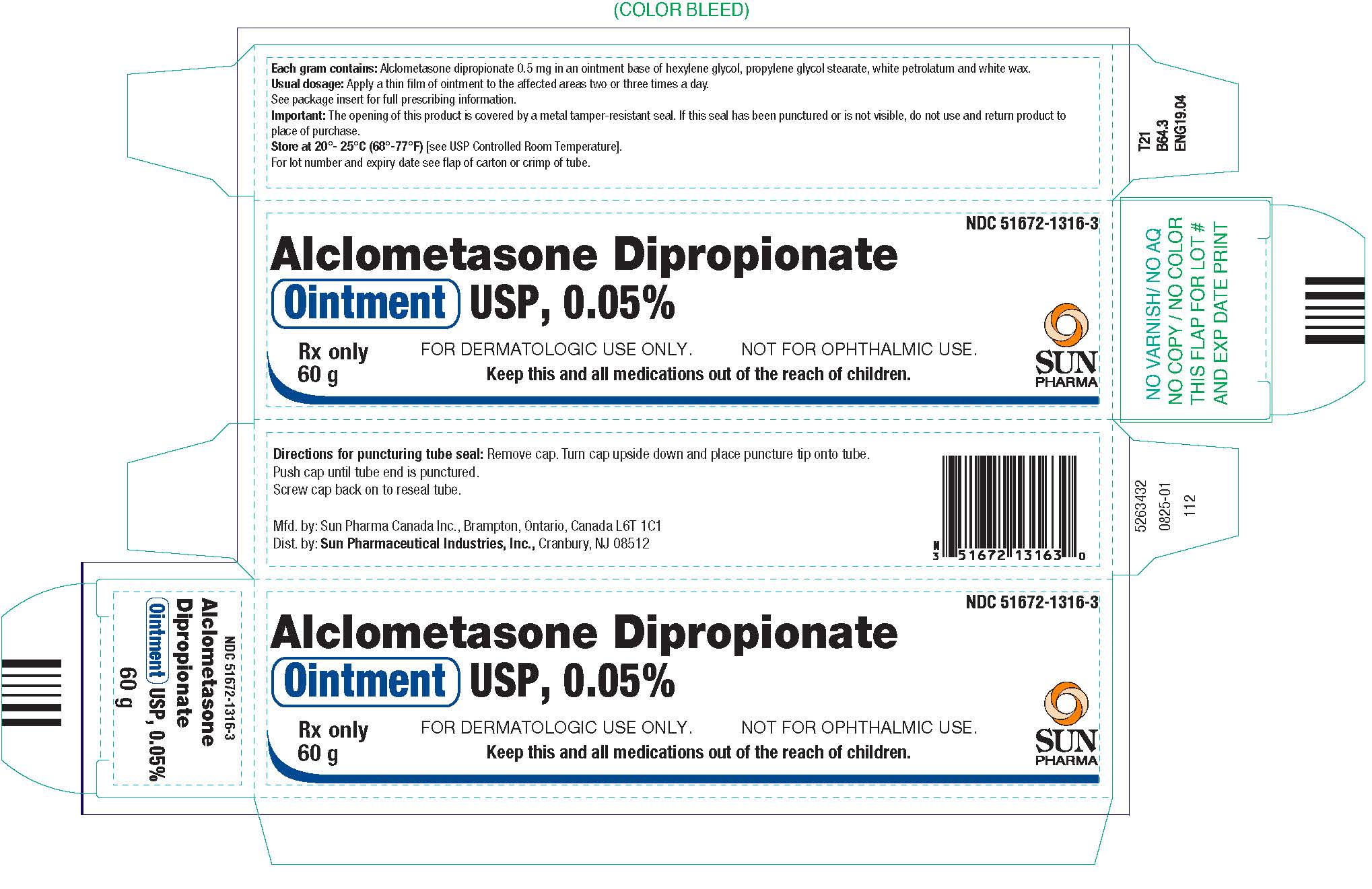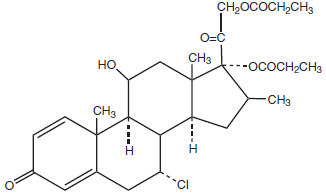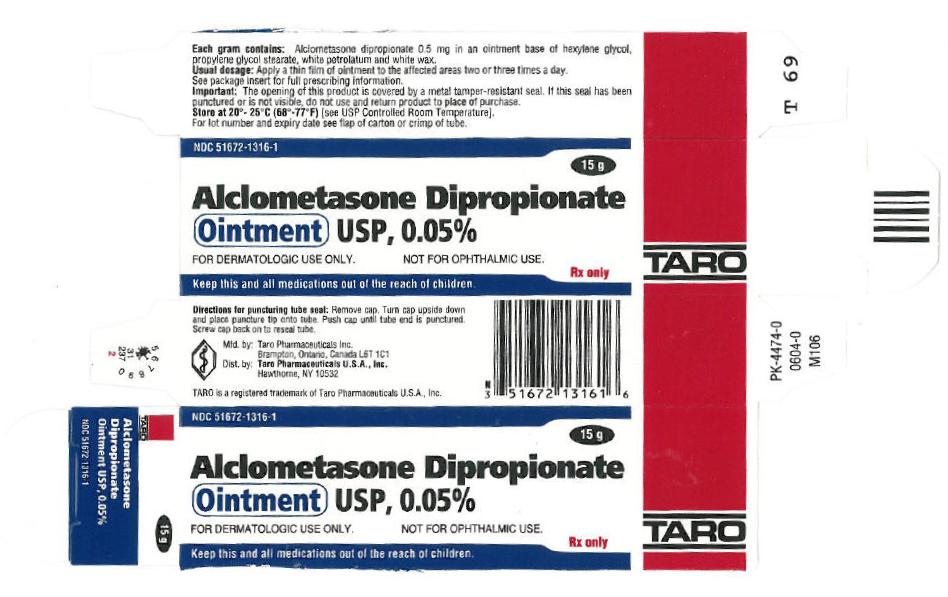 DRUG LABEL: Alclometasone Dipropionate
NDC: 51672-1316 | Form: OINTMENT
Manufacturer: Sun Pharmaceutical Industries, Inc.
Category: prescription | Type: HUMAN PRESCRIPTION DRUG LABEL
Date: 20250813

ACTIVE INGREDIENTS: ALCLOMETASONE DIPROPIONATE 0.5 mg/1 g
INACTIVE INGREDIENTS: HEXYLENE GLYCOL; PROPYLENE GLYCOL MONOPALMITOSTEARATE; PETROLATUM; WHITE WAX

Alclometasone Dipropionate
Ointment USP, 0.05%

For Dermatologic Use Only - - Not for Ophthalmic Use.

Rx Only

DESCRIPTION

Alclometasone Dipropionate Ointment USP, 0.05% contains alclometasone dipropionate (7α-chloro-11β,17,21-trihydroxy-16α-methylpregna-1,4-diene-3,20-dione 17,21-dipropionate), a synthetic corticosteroid for topical dermatologic use. The corticosteroids constitute a class of primarily synthetic steroids used topically as anti-inflammatory and antipruritic agents.

Chemically, alclometasone dipropionate is C28H37ClO7. It has the following structural formula:

Alclometasone dipropionate has the molecular weight of 521. It is a white powder, insoluble in water, slightly soluble in propylene glycol, and moderately soluble in hexylene glycol.

Each gram of alclometasone dipropionate ointment contains 0.5 mg of alclometasone dipropionate in an ointment base of hexylene glycol, propylene glycol stearate, white petrolatum and white wax.

CLINICAL PHARMACOLOGY

Like other topical corticosteroids, alclometasone dipropionate has anti-inflammatory, antipruritic, and vasoconstrictive properties. The mechanism of the anti-inflammatory activity of the topical steroids, in general, is unclear. However, corticosteroids are thought to act by the induction of phospholipase A2inhibitory proteins, collectively called lipocortins. It is postulated that these proteins control the biosynthesis of potent mediators of inflammation such as prostaglandins and leukotrienes by inhibiting the release of their common precursor, arachidonic acid. Arachidonic acid is released from membrane phospholipids by phospholipase A2.

Pharmacokinetics

The extent of percutaneous absorption of topical corticosteroids is determined by many factors, including the vehicle and the integrity of the epidermal barrier. Occlusive dressings with hydrocortisone for up to 24 hours have not been demonstrated to increase penetration; however, occlusion of hydrocortisone for 96 hours markedly enhances penetration. Topical corticosteroids can be absorbed from normal intact skin. Inflammation and/or other disease processes in the skin may increase percutaneous absorption. A study utilizing a radio labeled alclometasone dipropionate ointment formulation was performed to measure systemic absorption and excretion. Results indicated that approximately 3% of the steroid was absorbed during 8 hours of contact with intact skin of normal volunteers.

Studies performed with alclometasone dipropionate ointment indicate that this product is in the low to medium range of potency as compared with other topical corticosteroids.

INDICATIONS AND USAGE

Alclometasone Dipropionate Ointment USP, 0.05% is a low to medium potency corticosteroid indicated for the relief of the inflammatory and pruritic manifestations of corticosteroid-responsive dermatoses. Alclometasone dipropionate ointment may be used in pediatric patients 1 year of age or older, although the safety and efficacy of drug use for longer than 3 weeks have not been established (see PRECAUTIONS: Pediatric Use). Since the safety and efficacy of alclometasone dipropionate ointment has not been established in pediatric patients below 1 year of age, their use in this age-group is not recommended.

CONTRAINDICATIONS

Alclometasone Dipropionate Ointment USP, 0.05% is contraindicated in those patients with a history of hypersensitivity to any of the components in this preparation.

PRECAUTIONS

General

Systemic absorption of topical corticosteroids can produce reversible hypothalamic-pituitary-adrenal (HPA) axis suppression with the potential for glucocorticosteroid insufficiency after withdrawal of treatment. Manifestations of Cushing syndrome, hyperglycemia, and glucosuria can also be produced in some patients by systemic absorption of topical corticosteroids while on treatment. Patients applying a topical steroid to a large surface area or to areas under occlusion should be evaluated periodically for evidence of HPA axis suppression. This may be done by using the ACTH stimulation, A.M. plasma cortisol, and urinary free cortisol tests.

The effects of alclometasone dipropionate ointment on the HPA axis have been evaluated. In one study, alclometasone dipropionate ointment was applied to 30% of the body twice daily for 7 days, and occlusive dressings were used in selected patients either 12 hours or 24 hours daily. In another study, alclometasone dipropionate cream was applied to 80% of the body surface of normal subjects twice daily for 21 days with daily 12-hour periods of whole body occlusion. Average plasma and urinary free cortisol levels and urinary levels of 17-hydroxysteroids were decreased (about 10%), suggesting suppression of the HPA axis under these conditions. Plasma cortisol levels have also been demonstrated to decrease in pediatric patients treated twice daily for 3 weeks without occlusion.

If HPA axis suppression is noted, an attempt should be made to withdraw the drug, to reduce the frequency of application, or to substitute a less potent corticosteroid. Recovery of HPA axis function is generally prompt upon discontinuation of topical corticosteroids. Infrequently, signs and symptoms of glucocorticosteroid insufficiency may occur, requiring supplemental systemic corticosteroids. For information on systemic supplementation, see prescribing information for those products.

Pediatric patients may be more susceptible to systemic toxicity from equivalent doses due to their larger skin surface area to body mass ratios (see PRECAUTIONS: Pediatric Use).

If irritation develops, alclometasone dipropionate ointment should be discontinued and appropriate therapy instituted. Allergic contact dermatitis with corticosteroids is usually diagnosed by observing a failure to heal rather than noting a clinical exacerbation, as with most topical products not containing corticosteroids. Such an observation should be corroborated with appropriate diagnostic patch testing. If concomitant skin infections are present or develop, an appropriate antifungal or antibacterial agent should be used. If a favorable response does not occur promptly, use of alclometasone dipropionate ointment should be discontinued until the infection has been adequately controlled.

In a transgenic mouse study, chronic use of alclometasone dipropionate cream led to an increased number of animals with benign neoplasms of the skin at the treatment site (see PRECAUTIONS: Carcinogenesis, Mutagenesis, Impairment of Fertility). The clinical relevance of the findings in animal studies to humans is not clear.

Information for Patients

Patients using topical corticosteroids should receive the following information and instructions:

1. This medication is to be used as directed by the physician. It is for external use only. Avoid contact with the eyes.
2. This medication should not be used for any disorder other than that for which it was prescribed.
3. The treated skin area should not be bandaged, otherwise covered or wrapped so as to be occlusive, unless directed by the physician.
4. Patients should report to their physician any signs of local adverse reactions.
5. Parents of pediatric patients should be advised not to use alclometasone dipropionate ointment in the treatment of diaper dermatitis. Alclometasone dipropionate ointment should not be applied in the diaper area as diapers or plastic pants may constitute occlusive dressing (see DOSAGE AND ADMINISTRATION).
6. This medication should not be used on the face, underarms, or groin areas unless directed by the physician.
7. As with other corticosteroids, therapy should be discontinued when control is achieved. If no improvement is seen within 2 weeks, contact the physician.

Laboratory Tests

The following tests may be helpful in evaluating patients for HPA axis suppression:

- ACTH stimulation test
- A.M. plasma cortisol test
- Urinary free cortisol test

Carcinogenesis, Mutagenesis, Impairment of Fertility:

Systemic long-term animal studies have not been performed to evaluate the carcinogenic potential of alclometasone dipropionate. The effects of alclometasone dipropionate on mutagenesis or fertility have not been evaluated.

In a 26-week dermal carcinogenicity study conducted in transgenic (Tg.AC) mice, topical application once daily of both the vehicle cream and the 0.05% alclometasone dipropionate cream significantly increased the incidence of benign neoplasms of the skin in both sexes at the treatment site when compared to untreated controls. This suggests that the positive effect may be associated with the vehicle application. The clinical relevance of the findings in animals to humans is not clear.

Pregnancy

Teratogenic Effects

Pregnancy Category C

Corticosteroids have been shown to be teratogenic in laboratory animals when administered systemically at relatively low dosage levels. Some corticosteroids have been shown to be teratogenic after dermal application in laboratory animals. There are no adequate and well-controlled studies in pregnant women. Alclometasone dipropionate ointment should be used during pregnancy only if the potential benefit justifies the potential risk to the fetus.

Nursing Mothers

Systemically administered corticosteroids appear in human milk and could suppress growth, interfere with endogenous corticosteroid production, or cause other untoward effects. It is not known whether topical administration of topical corticosteroids could result in sufficient systemic absorption to produce detectable quantities in human milk. Because many drugs are excreted in human milk, caution should be exercised when alclometasone dipropionate ointment is administered to a nursing woman.

Pediatric Use

Alclometasone dipropionate ointment may be used with caution in pediatric patients 1 year of age or older, although the safety and efficacy of drug use for longer than 3 weeks have not been established. Use of alclometasone dipropionate ointment is supported by results from adequate and well-controlled studies in pediatric patients with corticosteroid-responsive dermatoses. Since the safety and efficacy of alclometasone dipropionate ointment has not been established in pediatric patients below 1 year of age, its use in this age-group is not recommended. Because of a higher ratio of skin surface area to body mass, pediatric patients are at a greater risk than adults of HPA axis suppression and Cushing syndrome when they are treated with topical corticosteroids. They are therefore also at greater risk of adrenal insufficiency during and/or after withdrawal of treatment. Adverse effects, including striae, have been reported with inappropriate use of topical corticosteroids in infants and children. Pediatric patients applying alclometasone dipropionate ointment to >20% of the body surface area are at higher risk for HPA axis suppression.

HPA axis suppression, Cushing syndrome, linear growth retardation, delayed weight gain, and intracranial hypertension have been reported in pediatric patients receiving topical corticosteroids. Manifestations of adrenal suppression in pediatric patients include low plasma cortisol levels and absence of response to ACTH stimulation. Manifestations of intracranial hypertension include bulging fontanelles, headaches, and bilateral papilledema.

Alclometasone dipropionate ointment should not be used in the treatment of diaper dermatitis.

Geriatric Use

A limited number of patients at or above 65 years of age have been treated with alclometasone dipropionate cream and ointment in US clinical trials. The number of patients is too small to permit separate analysis of efficacy and safety. No adverse events were reported with alclometasone dipropionate ointment in geriatric patients, and the single adverse reaction reported with alclometasone dipropionate cream in this population was similar to those reactions reported by younger patients. Based on available data, no adjustment of dosage of alclometasone dipropionate cream and ointment in geriatric patients is warranted.

ADVERSE REACTIONS

The following local adverse reactions have been reported with alclometasone dipropionate ointment in approximately 1% of patients: itching, burning, and erythema. The following additional local adverse reactions have been reported infrequently with topical corticosteroids, but may occur more frequently with the use of occlusive dressings. These reactions are listed in approximate decreasing order of occurrence: folliculitis, acneiform eruptions, hypopigmentation, perioral dermatitis, allergic contact dermatitis, secondary infection, skin atrophy, striae, and miliaria.

To report SUSPECTED ADVERSE REACTIONS, contact Sun Pharmaceutical Industries, Inc., at 1-866-923-4914 or FDA at 1-800-FDA-1088 or www.fda.gov/medwatch.

OVERDOSAGE

Topically applied alclometasone dipropionate ointment can be absorbed in sufficient amounts to produce systemic effects (see PRECAUTIONS).

DOSAGE AND ADMINISTRATION

Apply a thin film of Alclometasone Dipropionate Ointment USP, 0.05% to the affected skin areas two or three times daily; massage gently until the medication disappears.

Alclometasone dipropionate ointment may be used in pediatric patients 1 year of age or older. Safety and effectiveness of alclometasone dipropionate ointment in pediatric patients for more than 3 weeks of use have not been established. Use in pediatric patients under 1 year of age is not recommended.

As with other corticosteroids, therapy should be discontinued when control is achieved. If no improvement is seen within 2 weeks, reassessment of diagnosis may be necessary.

Alclometasone dipropionate ointment should not be used with occlusive dressings unless directed by a physician. Alclometasone dipropionate ointment should not be applied in the diaper area if the child still requires diapers or plastic pants as these garments may constitute occlusive dressing.

Geriatric Use

In studies where geriatric patients (65 years of age or older, see PRECAUTIONS) have been treated with alclometasone dipropionate ointment, safety did not differ from that in younger patients; therefore, no dosage adjustment is recommended.

HOW SUPPLIED

Alclometasone Dipropionate Ointment USP, 0.05% is supplied in 5 g (professional sample only), 15 g (NDC 51672-1316-1), 45 g (NDC 51672-1316-6), and 60 g (NDC 51672-1316-3) tubes.

STORAGE AND HANDLING

Store at 20°-25°C (68°-77°F)[see USP Controlled Room Temperature].

Mfd. by: Sun Pharma Canada Inc., Brampton, Ontario, Canada L6T 1C1

Dist. by: Sun Pharmaceutical Industries, Inc., Cranbury, NJ 08512
Revised: July 2025

5263352-0725-01

PRINCIPAL DISPLAY PANEL - 15 g Tube Carton

NDC 51672-1316-1

15 g

Alclometasone Dipropionate
Ointment USP, 0.05%